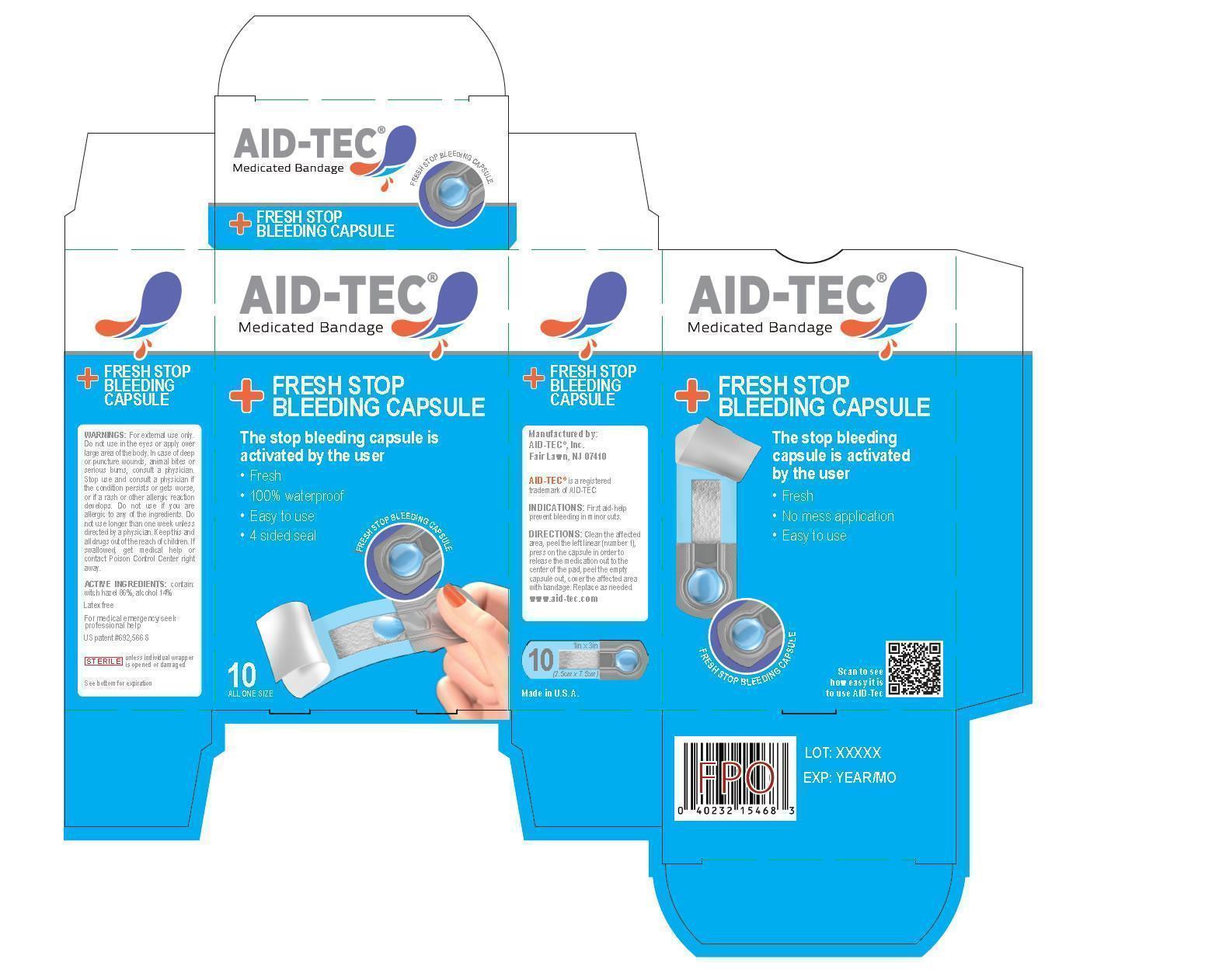 DRUG LABEL: Medicated Bandage
NDC: 69277-6132 | Form: TAPE
Manufacturer: Aid Tec Inc.
Category: otc | Type: HUMAN OTC DRUG LABEL
Date: 20151013

ACTIVE INGREDIENTS: WITCH HAZEL 88.2 g/100 g
INACTIVE INGREDIENTS: ALCOHOL 100 mL/100 g

SKIN PROTECTANT DRUG PRODUCTS FOR OVER-THE-COUNTER HUMAN USE